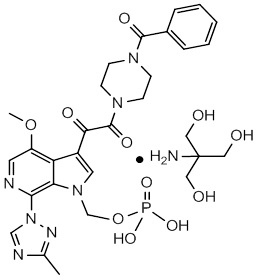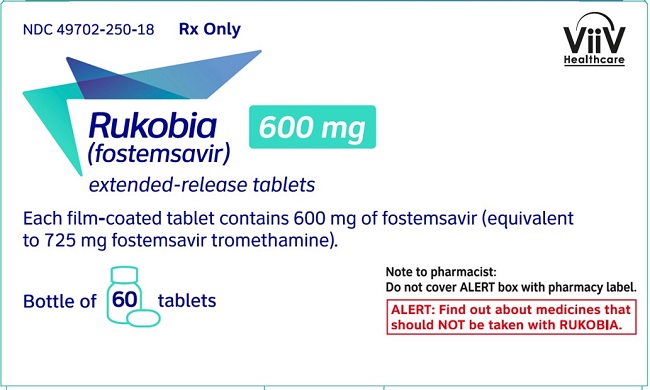 DRUG LABEL: Rukobia
NDC: 49702-250 | Form: TABLET, FILM COATED, EXTENDED RELEASE
Manufacturer: ViiV Healthcare Company
Category: prescription | Type: HUMAN PRESCRIPTION DRUG LABEL
Date: 20240213

ACTIVE INGREDIENTS: FOSTEMSAVIR TROMETHAMINE 600 mg/1 1
INACTIVE INGREDIENTS: SILICON DIOXIDE; HYDROXYPROPYL CELLULOSE, UNSPECIFIED; HYPROMELLOSE, UNSPECIFIED; MAGNESIUM STEARATE; FERRIC OXIDE RED; FERRIC OXIDE YELLOW; POLYETHYLENE GLYCOL, UNSPECIFIED; POLYVINYL ALCOHOL, UNSPECIFIED; TALC; TITANIUM DIOXIDE

HIGHLIGHTS OF PRESCRIBING INFORMATION

These highlights do not include all the information needed to use RUKOBIA safely and effectively. See full prescribing information for RUKOBIA.
RUKOBIA (fostemsavir) extended-release tablets, for oral use
Initial U.S. Approval: 2020

1 INDICATIONS AND USAGE

RUKOBIA, a human immunodeficiency virus type 1 (HIV-1) gp120-directed attachment inhibitor, in combination with other antiretroviral(s), is indicated for the treatment of HIV-1 infection in heavily treatment-experienced adults with multidrug-resistant HIV-1 infection failing their current antiretroviral regimen due to resistance, intolerance, or safety considerations. (1, 12.4)

2 DOSAGE AND ADMINISTRATION

One tablet taken twice daily with or without food. (2)

3 DOSAGE FORMS AND STRENGTHS

Extended-release tablets: 600 mg (3)

4 CONTRAINDICATIONS

- Hypersensitivity to fostemsavir or any of the components of the formulation. (4)
- Coadministration with strong cytochrome P450 (CYP)3A inducers as significant decreases in temsavir plasma concentrations may occur, which may result in loss of virologic response. (4)

5 WARNINGS AND PRECAUTIONS

- Immune reconstitution syndrome has been reported in patients treated with combination antiretroviral therapies. (5.1)
- QTc prolongation: Use RUKOBIA with caution in patients with a history of QTc prolongation or with relevant pre-existing cardiac disease or who are taking drugs with a known risk of Torsade de Pointes. (5.2)
- Elevations in hepatic transaminases in patients with hepatitis B (HBV) or C (HCV) virus co-infection: Elevations in hepatic transaminases were observed in a greater proportion of subjects with HBV and/or HCV co-infection compared with those with HIV mono-infection. (5.3)

6 ADVERSE REACTIONS

The most common adverse reaction (all grades) observed in ≥5% of subjects was nausea. (6.1)

To report SUSPECTED ADVERSE REACTIONS, contact ViiV Healthcare at 1-877-844-8872 or FDA at 1-800-FDA-1088 or www.fda.gov/medwatch.

7 DRUG INTERACTIONS

- See full prescribing information for complete list of significant drug interactions. (4, 7)
- Doses of oral contraceptives should not contain more than 30 mcg of ethinyl estradiol per day. (7.3)

FULL PRESCRIBING INFORMATION

1 INDICATIONS AND USAGE

RUKOBIA, in combination with other antiretroviral(s), is indicated for the treatment of human immunodeficiency virus type 1 (HIV-1) infection in heavily treatment-experienced adults with multidrug-resistant HIV-1 infection failing their current antiretroviral regimen due to resistance, intolerance, or safety considerations [see Clinical Studies (14)].

2 DOSAGE AND ADMINISTRATION

The recommended dosage of RUKOBIA is one 600-mg tablet taken orally twice daily with or without food [see Clinical Pharmacology (12.3)]. Swallow tablets whole. Do not chew, crush, or split tablets.

3 DOSAGE FORMS AND STRENGTHS

Each RUKOBIA extended-release tablet contains 600 mg of fostemsavir (equivalent to 725 mg of fostemsavir tromethamine). The tablets are beige, oval, film-coated, biconvex tablets, debossed with “SV 1V7” on one side.

4 CONTRAINDICATIONS

RUKOBIA is contraindicated in patients:

- with previous hypersensitivity to fostemsavir or any of the components of RUKOBIA.
- coadministered strong cytochrome P450 (CYP)3A inducers, as significant decreases in temsavir (the active moiety of fostemsavir) plasma concentrations may occur which may result in loss of virologic response. These drugs include, but are not limited to [see Drug Interactions (7), Clinical Pharmacology (12.3)]:
  - Androgen receptor inhibitor: Enzalutamide
  - Anticonvulsants: Carbamazepine, phenytoin
  - Antimycobacterial: Rifampin
  - Antineoplastic: Mitotane
  - Herbal product: St John’s wort (Hypericum perforatum)

5 WARNINGS AND PRECAUTIONS

5.1 Immune Reconstitution Syndrome

Immune reconstitution syndrome has been reported in patients treated with combination antiretroviral therapy, including RUKOBIA [see Adverse Reactions (6.1)]. During the initial phase of combination antiretroviral treatment, patients whose immune systems respond may develop an inflammatory response to indolent or residual opportunistic infections (such as Mycobacterium avium infection, cytomegalovirus, Pneumocystis jirovecii pneumonia [PCP], or tuberculosis), which may necessitate further evaluation and treatment.

Autoimmune disorders (such as Graves’ disease, polymyositis, Guillain-Barré syndrome, and autoimmune hepatitis) have also been reported to occur in the setting of immune reconstitution; however, the time to onset is more variable and can occur many months after initiation of treatment.

5.2 QTc Prolongation with Higher than Recommended Dosages

RUKOBIA at 2,400 mg twice daily, 4 times the recommended daily dose, has been shown to significantly prolong the QTc interval of the electrocardiogram [see Drug Interactions (7.4), Clinical Pharmacology (12.2)]. RUKOBIA should be used with caution in patients with a history of QTc interval prolongation, when coadministered with a drug with a known risk of Torsade de Pointes, or in patients with relevant pre-existing cardiac disease. Elderly patients may be more susceptible to drug-induced QT interval prolongation.

5.3 Elevations in Hepatic Transaminases in Patients with Hepatitis B or C Virus Co-Infection

Monitoring of liver chemistries is recommended in patients with hepatitis B (HBV) and/or C (HCV) virus co-infection. Elevations in hepatic transaminases were observed in a greater proportion of subjects with HBV and/or HCV co-infection compared with those with HIV mono-infection. Some of these elevations in transaminases were consistent with hepatitis B reactivation, particularly in the setting where anti-hepatitis therapy was withdrawn [see Adverse Reactions (6.1)]. Particular diligence should be applied in initiating or maintaining effective hepatitis B therapy (referring to treatment guidelines) when starting RUKOBIA in patients co-infected with hepatitis B.

5.4 Risk of Adverse Reactions or Loss of Virologic Response Due to Drug Interactions

The concomitant use of RUKOBIA and certain other drugs may result in known or potentially significant drug interactions, some of which may lead to [see Contraindications (4), Warnings and Precautions (5.2), Drug Interactions (7.3), Clinical Pharmacology (12.3)]:

- Loss of therapeutic effect of RUKOBIA and possible development of resistance due to reduced exposure of temsavir.
- Possible prolongation of QTc interval from increased exposure to temsavir [see Drug Interactions (7.4)].

See Table 3 for steps to prevent or manage these possible and known significant drug interactions, including dosing recommendations. Consider the potential for drug interactions prior to and during therapy with RUKOBIA, review concomitant medications during therapy with RUKOBIA, and monitor for the adverse reactions associated with the concomitant drugs.

6 ADVERSE REACTIONS

The following adverse reactions are discussed in greater detail in other sections of the labeling:

- Immune reconstitution syndrome [see Warnings and Precautions (5.1)].
- QTc prolongation [see Warnings and Precautions (5.2)].
- Elevations in hepatic transaminases in patients with hepatitis B or C virus co-infection [see Warnings and Precautions (5.3)].

6.1 Clinical Trials Experience

Because clinical trials are conducted under widely varying conditions, adverse reaction rates observed in the clinical trials of a drug cannot be directly compared with rates in the clinical trials of another drug and may not reflect the rates observed in practice.

A total of 620 subjects with HIV-1 infection received at least one dose of RUKOBIA as part of a controlled clinical trial.

The primary safety assessment of RUKOBIA is based on 96 weeks of data from a Phase 3 partially randomized, international, multicenter, double-blind, placebo-controlled trial (BRIGHTE) conducted in 371 heavily treatment-experienced adult subjects [see Clinical Studies (14)]. In the randomized cohort, 203 subjects received at least one dose of blinded RUKOBIA 600 mg twice daily and 69 subjects received placebo in addition to their current failing regimen for 8 days of functional monotherapy. Beyond Day 8, all randomized subjects except one received open-label RUKOBIA 600 mg twice daily plus an optimized background therapy (OBT). In the nonrandomized cohort, 99 subjects received open-label RUKOBIA 600 mg twice daily plus OBT from Day 1 onward.

A total of 370 subjects (271 randomized and 99 nonrandomized) received at least 1 dose of RUKOBIA 600 mg twice daily in the BRIGHTE trial. Overall, most (81%) of the adverse reactions reported with RUKOBIA were mild or moderate in severity. The proportion of subjects who discontinued treatment with RUKOBIA due to an adverse event was 7% at Week 96 (randomized: 5% and nonrandomized: 12%). The most common adverse events leading to discontinuation were related to infections (3% of subjects receiving RUKOBIA). Serious drug reactions occurred in 3% of subjects and included 3 cases of severe immune reconstitution inflammatory syndrome.

Data from the randomized cohort form the basis of the safety assessment of RUKOBIA because the presence of significant comorbid illness in the nonrandomized cohort (associated with advanced HIV infection) may confound the assessment of causality. Adverse reactions (all grades) reported in ≥2% of subjects in the randomized cohort in the Week 96 analysis are listed in Table 1.

Table 1. Adverse Reactionsa (Grades 1 to 4) Reported in ≥2% of Subjects Receiving RUKOBIA plus OBT in the BRIGHTE Trial, Randomized Cohort (Week 96 Analysis)
Adverse Reaction | RUKOBIA plus OBT; (n = 271)b
Nausea | 10%
Diarrhea | 4%
Headache | 4%
Abdominal painc | 3%
Dyspepsia | 3%
Fatigued | 3%
Rashe | 3%
Sleep disturbancef | 3%
Immune Reconstitution Inflammatory Syndrome | 2%
Somnolence | 2%
Vomiting | 2%
OBT = Optimized background therapy.
a Frequencies of adverse reactions are based on all treatment-emergent adverse events attributed to study drug by the investigator.
b Of the 272 subjects enrolled in the randomized cohort, 1 subject who received placebo withdrew from the trial prior to receiving RUKOBIA in the open-label phase of the trial.
c Includes pooled terms: abdominal discomfort, abdominal pain, and abdominal pain upper.
d Includes pooled terms: fatigue and asthenia.
e Includes pooled terms: rash, rash generalized, rash maculo-papular, rash pruritic, and dermatitis allergic.
f Includes pooled terms: insomnia, sleep deficit, sleep disorder, abnormal dreams.

Adverse reactions in the nonrandomized cohort were similar to those observed in the randomized cohort. The most common adverse reactions reported in nonrandomized subjects were fatigue (7%), nausea (6%), and diarrhea (6%).

Less Common Adverse Reactions

The following adverse reactions occurred in <2% of subjects receiving RUKOBIA in the randomized cohort of the BRIGHTE trial. These events have been included based on the assessment of potential causal relationship and were also reported in the nonrandomized cohort.

Cardiac Disorders: Electrocardiogram QT prolonged. All reports were asymptomatic.

Musculoskeletal Disorders: Myalgia.

Nervous System Disorders: Dizziness, dysgeusia, neuropathy peripheral (includes pooled terms: neuropathy peripheral and peripheral sensory neuropathy).

Skin and Subcutaneous Tissue Disorders: Pruritus.

Laboratory Abnormalities

Selected laboratory abnormalities (Grades 3 to 4) with a worsening grade from baseline and representing the worst-grade toxicity in ≥2% of subjects in the randomized cohort of the BRIGHTE trial are presented in Table 2.

Table 2. Selected Laboratory Abnormalities (Grades 3 to 4) Reported in ≥2% of Subjects in the Randomized Cohort Receiving RUKOBIA plus OBT in the BRIGHTE Trial (Week 96 Analysis)
Laboratory Parameter Preferred Term | RUKOBIA plus OBT (n = 271a)
ALT (>5.0 x ULN) | 5%
AST (>5.0 x ULN) | 4%
Direct bilirubin (>ULN)b | 7%
Bilirubin (≥2.6 x ULN) | 3%
Cholesterol (≥300 mg/dL)b | 5%
Creatinine (>1.8 x ULN or 1.5 x baseline) | 19%
Creatine kinase (≥10 x ULN) | 2%
Hemoglobin (<9.0 g/dL) | 6%
Hyperglycemia (>250 mg/dL) | 4%
Lipase (>3.0 x ULN) | 5%
LDL cholesterol (≥190 mg/dL) | 4%
Neutrophils (≤599 cells/mm^3) | 4%
Triglycerides (>500 mg/dL) | 5%
Urate (>12 mg/dL) | 3%
OBT = Optimized background therapy; ULN = Upper limit of normal.
a Percentages were calculated based on the number of subjects with post-baseline toxicity grades for each laboratory parameter (n = 221 for cholesterol and triglycerides, n = 216 for LDL cholesterol, and n = 268 for all other parameters).
b Grade 3 only (no Grade 4 values reported).

The incidence of selected laboratory abnormalities (Grades 3 to 4) in the nonrandomized cohort were overall consistent with those of the randomized cohort, with the exception of direct bilirubin (14% versus 7%), bilirubin (6% versus 3%), lipase (10% versus 5%), triglycerides (10% versus 5%), neutrophils (7% versus 4%), and leukocytes (6% versus 1%), respectively.

Changes in Serum Creatinine: Clinically relevant increases in serum creatinine have primarily occurred in patients with identifiable risk factors for reduced renal function, including pre-existing medical history of renal disease and/or concomitant medications known to cause increases in creatinine. A causal association between RUKOBIA and elevation in serum creatinine has not been established.

Changes in Direct Bilirubin: Increases in direct (conjugated) bilirubin have been observed following treatment with RUKOBIA (Table 2). Cases of clinical significance were uncommon and were confounded by the presence of intercurrent serious comorbid events (e.g., sepsis, cholangiocarcinoma, or other complications of viral hepatitis co-infection). In the remaining cases, elevations in direct bilirubin (without clinical jaundice) were typically transient, occurred without increases in liver transaminases, and resolved on continued RUKOBIA.

Changes in ALT and AST in Subjects with Hepatitis B and/or Hepatitis C Virus Co-Infection: A total of 29 subjects with Hepatitis B and/or Hepatitis C co-infection were enrolled in the BRIGHTE trial (randomized and nonrandomized cohorts combined). Grade 3 and 4 elevations in ALT and AST occurred in 14% of these subjects compared with 3% (ALT) and 2% (AST) of subjects without viral hepatitis co-infection. Some of these elevations in transaminases were consistent with hepatitis B reactivation particularly in the setting where anti-hepatitis therapy was withdrawn [see Warnings and Precautions (5.3)].

7 DRUG INTERACTIONS

7.1 Potential for RUKOBIA to Affect Other Drugs

Temsavir may increase plasma concentrations of grazoprevir or voxilaprevir to a clinically relevant extent due to organic anion transporting polypeptide (OATP)1B1/3 inhibition [see Drug Interactions (7.3)].

When RUKOBIA was coadministered with oral contraceptives, temsavir increased concentrations of ethinyl estradiol (Table 3) [see Drug Interactions (7.3), Clinical Pharmacology (12.3)].

7.2 Potential for Other Drugs to Affect RUKOBIA

Coadministration of RUKOBIA with rifampin, a strong CYP3A4 inducer, significantly decreases temsavir plasma concentrations. The use of RUKOBIA with drugs that are strong inducers of CYP3A4 can significantly decrease temsavir plasma concentrations which may lead to loss of virologic response [see Contraindications (4), Drug Interactions (7.3), Clinical Pharmacology (12.3)].

7.3 Established and Other Potentially Significant Drug Interactions

Information regarding potential drug interactions with RUKOBIA is provided in Table 3. These recommendations are based on either drug interaction trials or predicted interactions due to the expected magnitude of interaction and potential for serious adverse events or loss of efficacy [see Contraindications (4), Warnings and Precautions (5.4), Clinical Pharmacology (12.3)].

Table 3. Established and Other Potentially Significant Drug Interactionsa
Concomitant Drug Class: Drug Name | Effect on Concentration of Temsavir and/or Concomitant Drug | Clinical Comment
Androgen receptor inhibitor:; Enzalutamide | ↓Temsavir | Coadministration is contraindicated due to potential for loss of therapeutic effect to RUKOBIA [see Contraindications (4)].
Anticonvulsants:; Carbamazepine Phenytoin | ↓Temsavir | Coadministration is contraindicated due to potential for loss of therapeutic effect to RUKOBIA [see Contraindications (4)].
Antimycobacterial:; Rifampinb | ↓Temsavir | Coadministration is contraindicated due to potential for loss of therapeutic effect to RUKOBIA [see Contraindications (4)].
Antineoplastic:; Mitotane | ↓Temsavir | Coadministration is contraindicated due to potential for loss of therapeutic effect to RUKOBIA [see Contraindications (4)].
Herbal product:; St John’s wort (Hypericum perforatum) | ↓Temsavir
Hepatitis C virus direct-acting antivirals:; Grazoprevir Voxilaprevir | ↑Grazoprevir; ↑Voxilaprevir | Coadministration may increase exposures of grazoprevir or voxilaprevir; however, the magnitude of increase in exposure is unknown. Increased exposures of grazoprevir may increase the risk of ALT elevations. Use an alternative HCV regimen if possible.
Oral contraceptive:; Ethinyl estradiolb | ↑Ethinyl estradiol | Ethinyl estradiol daily dose should not exceed 30 mcg. Caution is advised particularly in patients with additional risk factors for thromboembolic events.
Statins:; Rosuvastatinb; Atorvastatin; Fluvastatin; Pitavastatin; Simvastatin | ↑Rosuvastatin; ↑Atorvastatin; ↑Fluvastatin; ↑Pitavastatin; ↑Simvastatin | Use the lowest possible starting dose for statins and monitor for statin-associated adverse events.
↑ = Increase; ↓ = Decrease; HCV = Hepatitis C virus.
a This table is not all inclusive.
b See Clinical Pharmacology (12.3) for magnitude of interaction.

7.4 Drugs that Prolong QT Interval

Coadministration of RUKOBIA with a drug with a known risk of Torsade de Pointes may increase the risk of Torsade de Pointes [see Warnings and Precautions (5.2), Clinical Pharmacology (12.2)]. Use RUKOBIA with caution when coadministered with drugs with a known risk of Torsade de Pointes.

7.5 Drugs without Clinically Significant Interactions with RUKOBIA

Based on drug interaction study results, the following drugs can be coadministered with RUKOBIA without a dose adjustment: atazanavir/ritonavir, buprenorphine/naloxone, cobicistat, darunavir/cobicistat, darunavir/ritonavir with and without etravirine, etravirine, famotidine, maraviroc, methadone, norethindrone, raltegravir, ritonavir, rifabutin with and without ritonavir, tenofovir disoproxil fumarate [see Clinical Pharmacology (12.3)].

8 USE IN SPECIFIC POPULATIONS

8.1 Pregnancy

Pregnancy Exposure Registry

There is a pregnancy exposure registry that monitors pregnancy outcomes in individuals exposed to RUKOBIA during pregnancy. Healthcare providers are encouraged to register patients by calling the Antiretroviral Pregnancy Registry (APR) at 1-800-258-4263.

Risk Summary

There are insufficient human data on the use of RUKOBIA during pregnancy to adequately assess a drug-associated risk of birth defects and miscarriage. In animal reproduction studies, oral administration of fostemsavir to pregnant rats and rabbits during organogenesis resulted in no adverse developmental effects at clinically relevant temsavir exposures (see Data).

The background risk for major birth defects and miscarriage for the indicated population is unknown. The background rate for major birth defects in a U.S. reference population of the Metropolitan Atlanta Congenital Defects Program (MACDP) is 2.7%. The estimated background rate of miscarriage in clinically recognized pregnancies in the U.S. general population is 15% to 20%.

Data

Animal Data: Fostemsavir was administered orally to pregnant rats (50, 200, 600 mg/kg/day) and rabbits (25, 50, or 100 mg/kg/day) during Gestation Days 6 to 15 (rat) and 7 to 19 (rabbit). No fetal abnormalities were observed at temsavir exposures of approximately 180 (rat) and 30 (rabbit) times those in humans at the maximum recommended human dose (MRHD). In rabbits, increased embryonic death associated with maternal toxicity was observed at temsavir exposures approximately 60 times those in humans at the MRHD. In a separate rat study conducted at drug exposures approximately 200 times those in humans at the MRHD, fetal abnormalities (cleft palate, open eyes, shortened snout, microstomia, misaligned mouth/jaw, and protruding tongue) and reductions in fetal body weights occurred in the presence of maternal toxicity.

In a rat pre- and postnatal development study, fostemsavir was administered orally at doses of 10, 50, or 300 mg/kg/day from Gestation Day 6 through Lactation Day 20. Reduced neonatal survival (7 to 14 days after birth) in the absence of other adverse fetal or neonatal effects was observed at maternal temsavir exposures approximately 130 times those in humans at the MRHD. No adverse fetal or neonatal effects were observed at maternal temsavir exposures approximately 35 times those in humans at the MRHD.

In a distribution study in pregnant rats, fostemsavir-related drug materials (i.e., temsavir and/or temsavir-derived metabolites) crossed the placenta and were detectable in fetal tissue.

8.2 Lactation

Risk Summary

It is not known whether RUKOBIA is present in human breast milk, affects human milk production, or has effects on the breastfed infant. When administered to lactating rats, fostemsavir-related drug was present in rat milk (see Data). When a drug is present in animal milk, it is likely that the drug will be present in human milk.

Potential risks of breastfeeding include: (1) HIV-1 transmission (in HIV-1–negative infants), (2) developing viral resistance (in HIV-1–positive infants), and (3) adverse reactions in a breastfed infant similar to those seen in adults.

Data

In a distribution study, fostemsavir-related drug materials (i.e., temsavir and/or temsavir-derived metabolites) were excreted in rat milk following a single dose of fostemsavir administered to lactating rats 7 to 9 days postpartum. In the pre- and postnatal development study in rats, temsavir was present in milk at concentrations similar to those measured in maternal plasma, as determined 11 days postpartum. In addition, lactational exposure was associated with reduced offspring survival at maternal temsavir exposures not thought to be clinically relevant.

8.4 Pediatric Use

The safety and effectiveness of RUKOBIA have not been established in pediatric patients.

8.5 Geriatric Use

Clinical trials of RUKOBIA did not include sufficient numbers of subjects aged 65 and older to determine whether they respond differently from younger subjects. In general, caution should be exercised in administration of RUKOBIA in elderly patients reflecting greater frequency of decreased hepatic, renal, or cardiac function, and of concomitant disease or other drug therapy [see Clinical Pharmacology (12.3)]. Elderly patients may be more susceptible to drug-induced QT interval prolongation [see Warnings and Precautions (5.2)].

8.6 Renal Impairment

No dosage adjustment is required for patients with renal impairment or those on hemodialysis [see Clinical Pharmacology (12.3)].

8.7 Hepatic Impairment

No dosage adjustment is required in patients with mild to severe hepatic impairment (Child-Pugh Score A, B, or C) [see Clinical Pharmacology (12.3)].

10 OVERDOSAGE

There is no known specific treatment for overdose with RUKOBIA. If overdose occurs, the patient should be monitored and standard supportive treatment applied as required, including monitoring of vital signs and ECG (QT interval), as well as observation of the clinical status of the patient. As fostemsavir is highly bound to plasma proteins, it is unlikely that it will be significantly removed by dialysis.

11 DESCRIPTION

Fostemsavir tromethamine is a prodrug of temsavir, an HIV-1 gp120-directed attachment inhibitor.

The chemical name of fostemsavir tromethamine is (3-((4-benzoyl-1-piperazinyl)(oxo)acetyl)-4-methoxy-7-(3-methyl-1H-1,2,4-triazol-1-yl)-1H-pyrrolo[2,3-c]pyridin-1-yl)methyl dihydrogen phosphate, 2-amino-2-(hydroxymethyl)-1,3-propanediol (1:1). The empirical formula is C25H26N7O8P•C4H11NO3. The molecular weight is 704.6 g/mol (583.5 as free acid). It has the following structural formula:

Fostemsavir tromethamine is a white powder and is soluble to greater than 250 mg/mL in aqueous solutions with a pH greater than 3.7.

RUKOBIA extended-release tablets are for oral administration. Each film-coated tablet contains 600 mg of fostemsavir (equivalent to 725 mg fostemsavir tromethamine), and the following inactive ingredients: colloidal silicon dioxide, hydroxypropyl cellulose, hypromellose, and magnesium stearate. The tablet film-coating contains the inactive ingredients iron oxide red, iron oxide yellow, polyethylene glycol, polyvinyl alcohol, talc, and titanium dioxide.

12 CLINICAL PHARMACOLOGY

12.1 Mechanism of Action

RUKOBIA is an HIV-1 antiretroviral agent [see Microbiology (12.4)].

12.2 Pharmacodynamics

Cardiac Electrophysiology

At therapeutic doses, RUKOBIA does not prolong the QT interval to any clinically relevant extent. At 4 times the recommended dose, the mean (upper 90% confidence interval) QTcF increase was 11.2 milliseconds (13.3 milliseconds). The observed increase in QTcF was temsavir concentration-dependent [see Warnings and Precautions (5.2)].

Exposure-Response Relationship

In the Phase 3 trial evaluating the recommended dosing regimen of RUKOBIA (600 mg twice daily) in subjects with multidrug resistant HIV-1 infection on their failing regimen, no relationship was observed between plasma temsavir Ctrough and change in plasma HIV-1 RNA from Day 1 to Day 8.

12.3 Pharmacokinetics

Fostemsavir is a prodrug of temsavir, its active moiety. Fostemsavir was generally not detectable in plasma following oral administration. However, temsavir was readily absorbed (Table 4). Following oral administration, increases in plasma temsavir exposure (Cmax and AUCtau) appeared dose proportional or slightly greater than dose proportional, over the range of 600 mg to 1,800 mg of RUKOBIA. The pharmacokinetics of temsavir following administration of RUKOBIA are similar between healthy and HIV-1–infected subjects.

Absorption, Distribution, Metabolism, and Excretion

The pharmacokinetic properties of temsavir following administration of RUKOBIA are provided in Table 4. The multiple-dose pharmacokinetic parameters are provided in Table 5.

Table 4. Pharmacokinetic Properties of Temsavir
Absorption
% Absolute bioavailabilitya | 26.9
Tmax (h) | 2.0
Effect of standard meal (relative to fasting)b | AUC ratio =1.10 (0.95, 1.26)
Effect of high-fat meal (relative to fasting)b | AUC ratio =1.81 (1.54, 2.12)
Distribution
% Plasma protein binding | 88.4; (primarily to HSA)
Blood-to-plasma ratio | 0.74
Steady-state volume of distribution (Vss, L)c | 29.5
Elimination
Major route of elimination | Metabolism
Clearance (CL and CL/Fd, L/h) | 17.9 and 66.4
Half-life (h) | 11
Metabolism
Metabolic pathwayse | Hydrolysis (esterases) [36.1% of oral dose]; Oxidation (CYP3A4) [21.2% of oral dose]; UGT [<1% of oral dose]
Excretion
% of dose excreted in urine (unchanged drug)f | 51 (<2)
% of dose excreted in feces (unchanged drug)f | 33 (1.1)
HSA = Human serum albumin; UGT = Uridine diphosphate glucuronosyl transferases.
a Dosing in absolute bioavailability study: single-dose administration of fostemsavir extended-release tablet 600 mg followed by single IV infusion of [^13C] temsavir 100 mcg.
b Geometric mean ratio (fed/fasted) in pharmacokinetic parameters and (90% confidence interval). Standard meal = ~423 kcal, 36% fat, 47% carbohydrates, and 17% protein. High-calorie/high-fat meal = ~985 kcal, 60% fat, 28% carbohydrates, and 12% protein.
c Volume of distribution at steady state (Vss) following IV administration.
d Apparent clearance.
e In vitro studies have shown that temsavir is biotransformed into 2 predominant circulating inactive metabolites: BMS-646915 (hydrolysis metabolite) and BMS-930644 (N-dealkylated metabolite).
f Dosing in mass balance study: single-dose administration of [^14C] fostemsavir oral solution 300 mg containing 100 microCi (3.7 MBq) of total radioactivity.

Table 5. Multiple-Dose Pharmacokinetic Parameters of Temsavir
Parameter Mean (CV%) | Temsavira
Cmax (ng/mL) | 1,770 (39.9)
AUCtau (ng.h/mL) | 12,900 (46.4)
Ctrough or C12 (ng/mL) | 478 (81.5)
CV = Coefficient of variation; Cmax = Maximum concentration; AUC = Area under the time concentration curve; C12 = Concentration at 12 hours.
a Based on population pharmacokinetic analyses in heavily treatment-experienced adult subjects with HIV-1 infection receiving 600 mg of RUKOBIA twice daily with or without food in combination with other antiretroviral drugs.

Specific Populations

No clinically significant differences in the pharmacokinetics of temsavir were observed based on age, sex, race/ethnicity (White, Black/African American, Asian, or other). The effect of hepatitis B and/or C virus co-infection on the pharmacokinetics of temsavir is unknown.

The pharmacokinetics of temsavir has not been studied in pediatric subjects and data are limited in subjects aged 65 years or older.

Population pharmacokinetic analyses of subjects with HIV-1 infection aged up to 73 years from studies with RUKOBIA indicated age had no clinically relevant effect on the pharmacokinetics of temsavir [see Use in Specific Populations (8.4, 8.5)].

Patients with Renal Impairment: No clinically relevant differences in total and unbound temsavir pharmacokinetics were observed in patients with mild to severe renal impairment. No clinically relevant differences in temsavir pharmacokinetics were observed in patients with end-stage renal disease (ESRD) on hemodialysis compared with the same patients with ESRD off hemodialysis. Temsavir was not readily cleared by hemodialysis with approximately 12.3% of the administered dose removed during the 4-hour hemodialysis session [see Use in Specific Populations (8.6)].

Patients with Hepatic Impairment: No clinically relevant differences in total and unbound temsavir pharmacokinetics were observed in patients with mild to severe hepatic impairment (Child-Pugh Score A, B, or C) [see Use in Specific Populations (8.7)].

Drug Interaction Studies

Temsavir is a substrate of CYP3A, esterases, P-glycoprotein (P-gp), and breast cancer resistance protein (BCRP). Drugs that induce or inhibit CYP3A, P-gp, and BCRP may affect temsavir plasma concentrations. Coadministration of fostemsavir with drugs that are strong CYP3A inducers result in decreased concentrations of temsavir. Coadministration of fostemsavir with drugs that are moderate CYP3A inducers and/or strong CYP3A, P-gp and/or BCRP inhibitors are not likely to have a clinically relevant effect on the plasma concentrations of temsavir.

Temsavir is an inhibitor of OATP1B1 and OATP1B3. Additionally, temsavir and 2 metabolites (Table 4) are inhibitors of BCRP. Thus, temsavir is expected to affect the pharmacokinetics of drugs that are substrates of OATP1B1/3 and/or BCRP [see Drug Interactions (7.3)].

At clinically relevant concentrations, significant interactions are not expected when RUKOBIA is coadministered with substrates of CYP1A2, 2A6, 2B6, 2C8, 2C9, 2C19, 2E1, 2D6, and 3A4; UGT1A1, 1A4, 1A6, 1A9, 2B7; P-gp; multidrug resistance protein (MRP)2; bile salt export pump (BSEP); sodium taurocholate co-transporting polypeptide (NTCP); multidrug and toxin extrusion protein (MATE)1/2K; organic anion transporters (OAT)1 and OAT3; organic cation transporters (OCT)1 and OCT2 based on in vitro and clinical drug interaction results (Table 6).

Drug interaction studies were performed with RUKOBIA and other drugs likely to be coadministered for pharmacokinetic interactions. The effects of temsavir on the pharmacokinetics of coadministered drugs are summarized in Table 6 and the effects of coadministration of other drugs on the pharmacokinetics of temsavir are summarized in Table 7.

Dosing recommendations as a result of established and other potentially significant drug-drug interactions with RUKOBIA are provided in Table 3 [see Drug Interactions (7.3)].

Table 6. Effect of Fostemsavira on the Pharmacokinetics of Coadministered Drugs
Coadministered Drug(s) and Dose(s) |  | Dose of RUKOBIA | n | Geometric Mean Ratio (90% CI) of Pharmacokinetic Parameters of Coadministered Drugs with/without RUKOBIA No Effect = 1.00
Coadministered Drug(s) and Dose(s) |  | Dose of RUKOBIA | n | Cmax | AUC | Ctau
Atazanavir + | 300 mg; once daily/ | 600 mg; twice daily | 18 | 1.03; (0.96, 1.10) | 1.09; (1.03, 1.15) | 1.19; (1.10, 1.30)
Ritonavir | 100 mg; once daily |  |  | 1.02; (0.96, 1.09) | 1.07; (1.03, 1.10) | 1.22; (1.12, 1.32)
Darunavir + | 600 mg; twice daily/ | 600 mg; twice daily | 13 | 0.98; (0.93, 1.04) | 0.94; (0.89, 1.00) | 0.95; (0.87, 1.04)
Ritonavir | 100 mg; twice daily |  |  | 1.00; (0.86, 1.16) | 1.15; (0.99, 1.33) | 1.19; (1.06, 1.35)
Darunavir + | 600 mg; twice daily/ | 600 mg; twice daily | 13 | 0.95; (0.90, 1.01) | 0.94; (0.89, 0.99) | 0.88; (0.77, 1.01)
Ritonavir + | 100 mg; twice daily/ |  |  | 1.14; (0.96, 1.35) | 1.09; (0.98, 1.22) | 1.07; (0.97, 1.17)
Etravirine | 200 mg; twice daily |  |  | 1.18; (1.10, 1.27) | 1.28; (1.20, 1.36) | 1.28; (1.18, 1.39)
Etravirine | 200 mg; twice daily | 600 mg; twice daily | 14 | 1.11; (1.04, 1.19) | 1.11; (1.05, 1.17) | 1.14; (1.08, 1.21)
Tenofovir disoproxil fumarate | 300 mg; once daily | 600 mg; twice daily | 18 | 1.18; (1.12, 1.25) | 1.19; (1.12, 1.25) | 1.28; (1.20, 1.38)
Rosuvastatin | 10-mg; single dose | 600 mg; twice daily | 18 | 1.78; (1.52, 2.09) | 1.69; (1.44, 1.99) | NA
Ethinyl estradiol/ | 0.030 mg; once daily/ | 600 mg; twice daily | 26 | 1.39; (1.28, 1.51) | 1.40; (1.29, 1.51) | NA
Norethindrone | 1.5 mg; once daily |  |  | 1.08; (1.01, 1.16) | 1.08; (1.03, 1.14) | NA
Maraviroc | 300 mg; twice daily | 600 mg; twice daily | 13 | 1.01; (0.84, 1.20) | 1.25; (1.08, 1.44) | 1.37; (1.26, 1.48)
Methadone | 40 to 120 mg | 600 mg | 16
R(-) Methadone | once daily | twice daily |  | 1.15; (1.11, 1.20) | 1.13; (1.07, 1.19) | 1.09; (1.01, 1.17)
S(+) Methadone |  |  |  | 1.15; (1.10, 1.19) | 1.15; (1.09, 1.21) | 1.10; (1.02, 1.19)
Total Methadone |  |  |  | 1.15; (1.11, 1.19) | 1.14; (1.09, 1.20) | 1.10; (1.02, 1.18)
Buprenorphine/; Naloxone | 8/2 to 24/6 mg; once daily | 600 mg; twice daily | 16
Buprenorphine |  |  |  | 1.24; (1.06, 1.46) | 1.30; (1.17, 1.45) | 1.39; (1.18, 1.63)
Norbuprenorph- ine |  |  |  | 1.24; (1.03, 1.51) | 1.39; (1.16, 1.67) | 1.36; (1.10, 1.69)
CI = Confidence Interval; n = Maximum number of subjects with data; NA = Not available.
AUC = AUCtau for repeat-dose studies and AUC(0-inf) for single-dose study.
a Temsavir is the active moiety.

Table 7. Effect of Coadministered Drugs on the Pharmacokinetics of Temsavira following Coadministration with Fostemsavir
Coadministered Drug(s); and Dose(s) |  | Dose of RUKOBIA | n | Geometric Mean Ratio (90% CI) of Temsavir Pharmacokinetic Parameters with/without Coadministered Drugs; No Effect = 1.00
Coadministered Drug(s); and Dose(s) |  | Dose of RUKOBIA | n | Cmax | AUC | Ctau
Atazanavir + | 300 mg; once daily/ | 600 mg; twice daily | 36 | 1.68; (1.58, 1.79) | 1.54; (1.44, 1.65) | 1.57; (1.28, 1.91)
Ritonavir | 100 mg; once daily
Darunavir + | 600 mg; twice daily/ | 600 mg; twice daily | 14 | 1.52; (1.28, 1.82) | 1.63; (1.42, 1.88) | 1.88; (1.09, 3.22)
Ritonavir | 100 mg; twice daily
Darunavir + | 600 mg; twice daily/ | 600 mg; twice daily | 18 | 1.53; (1.32, 1.77) | 1.34; (1.17, 1.53) | 1.33; (0.98, 1.81)
Ritonavir + | 100 mg; twice daily/
Etravirine | 200 mg; twice daily
Etravirine | 200 mg; twice daily | 600 mg; twice daily | 14 | 0.52; (0.45, 0.59) | 0.50; (0.44, 0.57) | 0.48; (0.32, 0.72)
Ritonavir | 100 mg; once daily | 600 mg; twice daily | 18 | 1.53; (1.31, 1.79) | 1.45; (1.29, 1.61) | 1.44; (1.00, 2.08)
Raltegravir + | 400 mg; twice daily/ | 1,200 mg; once daily | 17 | 1.23; (0.92, 1.64) | 1.07; (0.84, 1.34) | 1.17; (0.59, 2.32)
Tenofovir disoproxil fumarate | 300 mg; once daily | 1,200 mg; once daily | 17 | 1.23; (0.92, 1.64) | 1.07; (0.84, 1.34) | 1.17; (0.59, 2.32)
Rifabutin + | 150 mg; once daily/ | 600 mg; twice daily | 23 | 1.50; (1.38, 1.64) | 1.66; (1.52, 1.81) | 2.58; (1.95, 3.42)
Ritonavir | 100 mg; once daily | 600 mg; twice daily | 23 | 1.50; (1.38, 1.64) | 1.66; (1.52, 1.81) | 2.58; (1.95, 3.42)
Rifabutin | 300 mg; once daily | 600 mg; twice daily | 22 | 0.73; (0.65, 0.83) | 0.70; (0.64, 0.76) | 0.59; (0.46, 0.77)
Rifampin | 600 mg; once daily | 1,200-mg; single dose | 15 | 0.24; (0.21, 0.28) | 0.18; (0.16, 0.2) | NA
Cobicistat | 150 mg; once daily | 600 mg; twice daily | 16 | 1.71; (1.54, 1.90) | 1.93; (1.75, 2.12) | 2.36; (2.03, 2.75)
Darunavir + | 800 mg; once daily/ | 600 mg; twice daily | 15 | 1.79; (1.62, 1.98) | 1.97; (1.78, 2.18) | 2.24; (1.75, 2.88)
Cobicistat | 150 mg; once daily | 600 mg; twice daily | 15 | 1.79; (1.62, 1.98) | 1.97; (1.78, 2.18) | 2.24; (1.75, 2.88)
Tenofovir disoproxil fumarate | 300 mg; once daily | 600 mg; twice daily | 18 | 0.99; (0.86, 1.13) | 1.00; (0.91, 1.11) | 1.13; (0.77, 1.66)
Maraviroc | 300 mg; twice daily | 600 mg; twice daily | 14 | 1.13; (0.96, 1.32) | 1.10; (0.99, 1.23) | 0.90; (0.69, 1.17)
Famotidine | 40-mg; single dose | 600-mg; single dose | 24 | 1.01; (0.85, 1.21) | 1.04; (0.87, 1.25) | 0.90; (0.64, 1.28)
CI = Confidence Interval; n = Maximum number of subjects with data; NA = Not available.
AUC = AUCtau for repeat-dose studies and AUC(0-inf) for single-dose study.
Ctau = C12 for single-dose study.
a Temsavir is the active moiety.

12.4 Microbiology

Mechanism of Action

Fostemsavir is a prodrug without significant biochemical or antiviral activity that is hydrolyzed to the active moiety, temsavir, which is an HIV-1 attachment inhibitor. Temsavir binds directly to the gp120 subunit within the HIV-1 envelope glycoprotein gp160 and selectively inhibits the interaction between the virus and cellular CD4 receptors, thereby preventing attachment. Additionally, temsavir can inhibit gp120-dependent post-attachment steps required for viral entry into host cells. Temsavir inhibited the binding of soluble CD4 to surface immobilized gp120 with an IC50 value of 14 nM using an enzyme-linked immunosorbent assay (ELISA).

Antiviral Activity in Cell Culture

Temsavir exhibited antiviral activity against 3 CCR5-tropic laboratory strains of subtype B HIV‑1, with EC50 values ranging from 0.4 to 1.7 nM. The range of susceptibility to temsavir was broader for CXCR4-tropic laboratory strains with 2 strains having EC50 values of 0.7 and 2.2 nM and 3 strains having EC50 values of 14.8, 16.2, and >2,000 nM. Antiviral activity of temsavir against HIV-1 subtype B clinical isolates varied depending on tropism with median EC50 values against the CCR5-tropic viruses, CXCR4-tropic viruses, and dual/mixed viruses of 3.7 nM (n = 9; range: 0.3 to 345 nM), 40.9 nM (n = 4; range: 0.6 to >2,000 nM), and 0.8 nM (n = 2; range: 0.3 to 1.3), respectively, showing a broad range of EC50 values for temsavir across the different tropic strains.

Analysis of data from 1,337 clinical samples from the fostemsavir clinical development program (881 subtype B samples, 156 subtype C samples, 43 subtype A samples, 17 subtype A1 samples, 48 subtype F1 samples, 29 subtype BF1 samples, 19 subtype BF samples, 5 CRF01_AE samples, and 139 other) showed temsavir susceptibility is highly variable across subtypes with a wide range in EC50 values from 0.018 nM to >5,000 nM. The majority of subtype B isolates (84%, 740/881) had EC50 values below 10 nM, with 6% of isolates having EC50 values >100 nM. Of all isolates from all subtypes tested, 9% exhibited EC50 values >100 nM. Subtypes BF, F1 and BF1 had higher proportions (21% to 38%) of isolates with EC50 values >100 nM, and all 5 of 5 subtype AE isolates had EC50 values >100 nM. From an additional panel of clinical isolates with non-B subtypes, temsavir EC50 values were greater than the upper limits of the concentrations tested (>1,800 nM) in all subtype E (AE; 3 of 3), Group O (2 of 2), and HIV-2 (1 of 1) isolates, and some subtype D (1 of 4) and subtype G (1 of 3) isolates.

Reduced Antiviral Activity against Subtype AE

Temsavir showed reduced antiviral activity against 14 different subtype AE isolates in peripheral blood mononuclear cell (PBMC) assays and the Phenosense Entry assay indicating that subtype AE (or E) viruses are inherently less sensitive to temsavir. Genotyping of subtype AE viruses identified polymorphisms at amino acid positions S375H and M475I in gp120, which have been associated with reduced susceptibility to fostemsavir. Subtype AE is a predominant subtype in Southeast Asia, but it is not found in high frequencies elsewhere throughout the world.

There were 2 subjects with subtype AE virus at screening in the randomized cohort of the clinical trial. One subject (EC50 fold change >4,747-fold and gp120 substitutions at S375H and M475I at baseline) did not respond to RUKOBIA at Day 8. A second subject (EC50 fold change 298-fold and gp120 substitution at S375N at baseline) received placebo during functional monotherapy. Both subjects were virologically suppressed at Week 96 while receiving OBT (with dolutegravir) plus RUKOBIA.

Antiviral Activity in Combination with Other Antiviral Agents

The antiviral activity of temsavir was not antagonistic in cell culture when combined with the CD4-directed post-attachment HIV-1 inhibitor ibalizumab, the CCR5 co-receptor antagonist maraviroc, the gp41 fusion inhibitor enfuvirtide, integrase strand transfer inhibitors (INSTIs) (dolutegravir, raltegravir), non-nucleoside reverse transcriptase inhibitors (NNRTIs) (delavirdine, efavirenz, nevirapine, rilpivirine), nucleoside reverse transcriptase inhibitors (NRTIs) (abacavir, didanosine, emtricitabine, lamivudine, stavudine, tenofovir disoproxil fumarate, zidovudine), or protease inhibitors (PIs) (amprenavir, atazanavir, darunavir, indinavir, lopinavir, nelfinavir, ritonavir, saquinavir). In addition, temsavir antiviral activity was not antagonistic in cell culture with the anti-HBV drug entecavir and the anti-HCV drug ribavirin.

Resistance in Cell Culture

HIV-1 variants with reduced susceptibility to temsavir were selected following 14 to 49 days passage in cell culture of NL4-3, LAI, and BaL viruses in a T-cell line. Selected viruses exhibited 18- to 159-fold decreased temsavir susceptibility and genotypic analysis identified the following emerging amino acid substitutions in gp120: L116P/Q, L175P, A204D, V255I, A281V, M426L, M434I, and M475I (S375 substitutions were identified based on in vivo data with a related attachment inhibitor). In general, most substitutions mapped to the conserved regions (C1, C2, C4, and C5) of the gp120 envelope, confirming temsavir targets the viral envelope protein during infection.

Single-substitution recombinant viruses at these amino acid positions were engineered into the HIV-1 LAI viral background and the resultant recombinants demonstrated reduced susceptibility to temsavir (L116P [>340-fold], A204D [>340-fold], S375M [47-fold], S375V [5.5-fold], S375Y [>10,000-fold], M426L [81-fold], M426V [3.3-fold], M434I [11-fold], M434T [15-fold], M475I [5-fold], M475L [17-fold], and M475V [9.5-fold]).

Temsavir remained active against laboratory-derived CD4-independent viruses and temsavir-resistant viruses showed no evidence of a CD4-independent phenotype. Therefore, treatment with RUKOBIA is unlikely to promote resistance to temsavir via generation of CD4-independent virus.

Response at Day 8 by Genotype

The effect of the gp120 resistance-associated polymorphisms (RAPs) on response to fostemsavir functional monotherapy at Day 8 was assessed in an as-treated analysis by censoring the subjects who had a >0.4 log10 decline in HIV-1 RNA from screening to baseline or <400 copies/mL at screening (n = 47 subjects were censored). The presence of gp120 RAPs at key sites S375, M426, M434, or M475 was associated with a lower overall decline in HIV-1 RNA and fewer subjects achieving >0.5 log10 decline in HIV-1 RNA compared with subjects with no changes at these sites (Table 8). However, the presence of the gp120 RAPs did not preclude some subjects from achieving a response of >0.5 log10 copies/mL at Day 8. Baseline gp120 RAPs most associated with decreased response of <0.5 log10 copies/mL at Day 8 were S375M, M426L, and M475V (Table 8). There was no difference in response rates and median decline in viral load for subjects with more than one gp120 RAP.

Table 8. Outcome of Randomized Fostemsavir Cohort by Presence of Screening gp120 RAPs (As-Treated Analysisa)
Envelope RAPs | Response Rate at Day 8; (>0.5 log10 decline); n = 151 | Median Log10 Decline in Viral Load:; Baseline to Day 8; n = 151
Overall | 107/151 (71%) | 1.05
No gp120 RAPs (at predefined sites) | 70/83 (84%) | 1.11
Predefined gp120 RAPs:
S375I/M/N/T, M426L, M434I, or M475I/V | 37/68 (54%) | 0.66
S375M | 1/5 (20%) | 0.32
M426L | 6/17 (35%) | 0.19
M434I | 3/6 (50%) | 0.66
M475V | 0/1 (0%) | 0
1 gp120 RAP | 38/62 (61%) | 1.03
2 or 3 gp120 RAPs | 18/26 (69%) | 1.09
RAPs = Resistance-associated polymorphisms.
a Removed subjects who had <400 copies/mL at screening or >0.4 log10 decline from screening to baseline.

Response at Day 8 by Phenotype

The fold change in susceptibility to temsavir for subject isolates at screening was highly variable ranging from 0.06 to 6,651. The effect of screening fostemsavir phenotype on response of >0.5 log10 decline at Day 8 was assessed in the as-treated analysis. The majority of these subjects (55%, 83/151) had a screening temsavir EC50 fold change normalized to a reference virus of <2‑fold. The response rate for fostemsavir phenotypes ≤2 was 80% (66/83) (Table 9). Response rates for fostemsavir phenotypic fold changes of >2 to 200 were moderately decreased to 69% (29/42). Phenotypic fold changes of >200 resulted in lower response rates to fostemsavir (29%, 5/17). Five subjects, despite having >200-fold decreased fostemsavir susceptibility and the presence of screening gp120 RAPs, had over 1 log10 declines in HIV-1 RNA at Day 8. Lack of resistance to background drugs or higher fostemsavir concentrations do not explain the >1 log10 response of these 5 subjects.

Table 9. Response Rate of Randomized Fostemsavir Cohort (>0.5 Log10 Decline Day 8) by Screening Phenotype
Fostemsavir Phenotypic Fold Change | Response Rate at Day 8; (>0.5 log10 decline); As-Treated Analysisa; n = 151
Not Reported | 9
0 - 2 | 66/83 (80%)
>2 - 10 | 17/25 (68%)
10 - 200 (Range 11 - 104) | 12/17 (71%)
>200 (Range 234 - 6,651) | 5/17 (29%)
a Removed subjects who had <400 copies/mL at screening or >0.4 log10 decline from screening to baseline.

Resistance in Clinical Subjects

The percentage of subjects who experienced virologic failure through the Week 96 analysis was 25% (69/272) in the randomized cohort (including 25% [51/203] among subjects who received blinded fostemsavir functional monotherapy and 26% [18/69] among subjects who received blinded placebo during the 8‑day double-blind period) (Table 10). Virologic failure = confirmed ≥400 copies/mL after prior confirmed suppression to <400 copies/mL, ≥400 copies/mL at last available prior to discontinuation, or >1 log10 copies/mL increase in HIV-1 RNA at any time above nadir level (≥40 copies/mL). Overall, 55% (29/53) of evaluable subjects with virologic failure in the randomized cohorts had treatment-emergent gp120 genotypic substitutions at 4 key sites (S375, M426, M434, and M475) (Table 10). One subject in the randomized cohort receiving fostemsavir plus OBT (but did not receive ibalizumab) experienced loss of virologic response and had an emergent K202E substitution in gp120. The glutamic acid (E) substitution at position 202 in gp120 was found to confer reduced susceptibility to both fostemsavir and ibalizumab (see Cross-Resistance).

The median temsavir EC50 fold change at failure in randomized evaluable subject isolates with emergent gp120 substitutions at positions 375, 426, 434, or 475 (n = 29) was 1,142-fold. In randomized evaluable subject isolates with no emergent gp120 substitutions at those positions (n = 24), the median temsavir EC50 fold change at failure was 0.92-fold.

Forty-one percent (28/69) of the virologic failures in the randomized groups combined had genotypic or phenotypic resistance to at least one drug in the OBT at screening, and 48% (31/64) of the virologic failures with post-baseline data had emergent resistance to at least one drug in the OBT.

Rates of virologic failure were higher in the nonrandomized cohort at 51% (50/99) (Table 10). While the proportion of virologic failures with gp120 RAPs at screening was similar between subjects in the randomized and nonrandomized cohorts, the proportion of subjects with emergent gp120 resistance-associated substitutions at the time of failure was higher among nonrandomized subjects (Table 10). The median temsavir EC50 fold change at failure in nonrandomized evaluable subject isolates with emergent substitutions at positions 375, 426, 434, or 475 (n = 33) was 4,216-fold and was 767-fold among failure subject isolates without emergent resistance-associated substitutions (n = 12).

Consistent with the nonrandomized group of subjects having fewer antiretroviral options, 90% (45/50) of the virologic failures in this group had genotypic or phenotypic resistance to at least one drug in the OBT at screening, and 55% (27/49) of the virologic failures with post-baseline data in the nonrandomized group had emergent resistance to at least one drug in the OBT.

Table 10. Virologic Failures in BRIGHTE Trial
 | Randomized; Cohort Total | Nonrandomized Cohort Total
Number of virologic failures | 69/272 (25%) | 50/99 (51%)
With gp120 RAPs at screening (of those with genotypic data) | 43/68 (63%) | 26/48 (54%)
Virologic failures with post-baseline data | 53 | 45
With emergent gp120 RAS | 29/53 (55%) | 33/45 (73%)
S375H/I/M/N/T | 19/53 (36%) | 21/45 (47%)
M426L/I | 18/53 (34%) | 23/45 (51%)
M434I/L | 6/53 (11%) | 5/45 (11%)
M475I/L/V | 8/53 (15%) | 5/45 (11%)
RAPs = Resistance-associated polymorphisms; RAS = Resistance-associated substitutions.

Cross-Resistance

There was no evidence of cross-resistance to representative agents from other antiretroviral (ARV) classes including INSTIs, NNRTIs, NRTIs, and PIs. Temsavir retained wild-type activity against viruses resistant to the INSTI raltegravir, the NNRTIs (efavirenz, rilpivirine), the NRTIs (abacavir, lamivudine, tenofovir, zidovudine), and the PIs (atazanavir and darunavir).

Additionally, the INSTI raltegravir, the NNRTIs (efavirenz, rilpivirine), the NRTIs (abacavir, tenofovir), and the PIs (atazanavir, darunavir), retained activity against site-directed mutants with reduced temsavir susceptibility (i.e., S375M, M426L, or M426L plus M475I).

Both the CD4-directed post-attachment inhibitor ibalizumab and the gp120-directed attachment inhibitor fostemsavir develop reduced susceptibility in gp120. Ibalizumab retained activity against site-directed mutants that had reduced susceptibility to temsavir (i.e., S375M, M426L, or M426L plus M475I). Temsavir was active against several ibalizumab-resistant viruses. However, HIV-1 gp120 E202 was identified as a treatment-emergent substitution seen in a single subject in BRIGHTE that can reduce susceptibility to temsavir, and, depending on the sequence context of the envelope, can result in reduced susceptibility to ibalizumab.

Temsavir was active against viruses with resistance to enfuvirtide. Temsavir had reduced activity against some CCR5-tropic, maraviroc-resistant viruses, but no absolute correlation between maraviroc resistance and reduced temsavir susceptibility has been identified. Maraviroc and enfuvirtide retained activity against clinical envelopes that had reduced susceptibility to temsavir and contained S375H, M426L, or M426L plus M475I substitutions.

13 NONCLINICAL TOXICOLOGY

13.1 Carcinogenesis, Mutagenesis, Impairment of Fertility

Carcinogenesis

In a 2-year carcinogenicity study conducted in rats and a 26-week carcinogenicity study conducted in transgenic mice, fostemsavir produced no statistically significant increases in tumors over controls. The maximum daily exposures in rats were approximately 5 times (males) and 16 times (females) greater than those in humans at the MRHD.

Mutagenesis

Fostemsavir was not genotoxic in the bacterial reverse mutation assay (Ames test in Salmonella and E. coli), a chromosome aberration test in human lymphocytes, and rat bone marrow micronucleus test.

Impairment of Fertility

Oral administration of fostemsavir had no adverse effects on male or female fertility in rats at exposures approximately 10 times (males) and 186 times (females) of those in humans at the MRHD. At higher exposures (>80 times those in humans at the MRHD) in male rats, decreases in prostate gland/seminal vesicle weights, sperm density/motility, and increased abnormal sperm were observed.

14 CLINICAL STUDIES

The efficacy of RUKOBIA in heavily treatment-experienced adult subjects with HIV-1 infection is based on 96-week data from a Phase 3, partially-randomized, international, double-blind, placebo-controlled trial (BRIGHTE [NCT02362503]).

The BRIGHTE trial was conducted in 371 heavily treatment-experienced subjects with multi-class HIV-1 resistance. All subjects were required to have a viral load ≥400 copies/mL and ≤2 classes of antiretroviral medications remaining at baseline due to resistance, intolerability, contraindication, or other safety concerns. Subjects were enrolled in either a randomized or nonrandomized cohort defined as follows:

- Within the randomized cohort (n = 272), subjects had 1, but no more than 2, fully active and available antiretroviral agent(s) at screening which could be combined as part of an efficacious background regimen. Randomized subjects received either blinded RUKOBIA 600 mg twice daily (n = 203) or placebo (n = 69) in addition to their current failing regimen for 8 days of functional monotherapy. Beyond Day 8, randomized subjects received open-label RUKOBIA 600 mg twice daily plus an investigator-selected OBT. This cohort provides primary evidence of efficacy of RUKOBIA.
- Within the nonrandomized cohort (n = 99), subjects had no fully active and approved antiretroviral agent(s) available at screening. Nonrandomized subjects were treated with open-label RUKOBIA 600 mg twice daily plus OBT from Day 1 onward. The use of an investigational drug(s) as a component of the OBT was permitted in the nonrandomized cohort.

Overall, the majority of subjects were male (78%), White (70%), and the median age was 49 years (range: 17 to 73 years). At baseline, the median HIV-1 RNA was 4.6 log10 copies/mL and the median CD4+ cell count was 80 cells/mm^3 (100 and 41 cells/mm^3 for randomized and nonrandomized subjects, respectively). Seventy-five percent (75%) of all treated subjects had a CD4+ cell count <200 cells/mm^3 at baseline (with 30% <20 cells/mm^3). Overall, 86% had a history of Acquired Immune Deficiency Syndrome (AIDS) and 8% had a history of hepatitis B and/or C virus co-infection at baseline. Seventy one percent (71%) of subjects had been treated for HIV for >15 years; 85% had been exposed to ≥5 different HIV treatment regimens upon entry into the trial.

Fifty-two percent (52%) of subjects in the randomized cohort had 1 fully active agent within their initial failing background regimen, 42% had 2, and 6% had no fully active agent. Within the nonrandomized cohort, 81% of subjects had no fully active agent(s) in their original regimen and 19% had 1 fully active agent, including 15% (n = 15) who received ibalizumab, which was an investigational agent at the time of the BRIGHTE trial start-up.

Randomized Cohort

The primary efficacy endpoint was the adjusted mean decline in HIV-1 RNA from Day 1 to Day 8 with RUKOBIA versus placebo in the randomized cohort. The results of the primary endpoint analysis demonstrated superiority of RUKOBIA compared with placebo, as shown in Table 11.

Table 11. Plasma HIV-1 RNA Log10 (copies/mL) Change from Day 1 to Day 8 (Randomized Cohort) in BRIGHTE Trial – ITT-E Population
 | RUKOBIA 600 mg Twice Daily; (n = 201a) | Placebo; (n = 69)
Adjusted Meanb (95% CI) | -0.791 (-0.885, -0.698) | -0.166 (-0.326, -0.007)
Differencec (95% CI) | -0.625 (-0.810, -0.441)d | -
a Two subjects who received RUKOBIA with missing Day 1 HIV-1 RNA values were not included in the analysis.
b Mean adjusted by Day 1 log10 HIV-1 RNA.
c Difference: RUKOBIA minus placebo.
d P-value <0.0001 for the adjusted and unadjusted mean difference of viral load change from baseline for RUKOBIA compared with placebo.

At Day 8, 65% (131/203) and 46% (93/203) of subjects who received RUKOBIA had a reduction in viral load from baseline >0.5 log10 copies/mL and >1 log10 copies/mL, respectively, compared with 19% (13/69) and 10% (7/69) of subjects, respectively, in the placebo group.

By subgroup analysis, randomized subjects who received RUKOBIA with baseline HIV-1 RNA >1,000 copies/mL achieved a mean decline in viral load of 0.86 log10 copies/mL at Day 8 compared with 0.20 log10 copies/mL in subjects treated with blinded placebo. Subjects with baseline HIV-1 RNA ≤1,000 copies/mL achieved a mean decline in viral load of 0.22 log10 copies/mL at Day 8 compared with a mean increase of 0.10 log10 copies/mL in subjects treated with blinded placebo.

Virologic outcomes by ITT-E Snapshot Analysis at Weeks 24 and 96 in the BRIGHTE trial are shown in Table 12 and Table 13 for the randomized cohort. There was considerable variability in the number of antiretrovirals (fully active and otherwise) included in OBT regimens. The majority of subjects (84%) received dolutegravir as a component of OBT, of which approximately half (51% overall) also received darunavir with ritonavir or cobicistat. Virologic outcomes by ITT-E Snapshot Analysis at Week 48 were consistent with those observed at Week 24.

Table 12. Virologic Outcomes (HIV-1 RNA <40 copies/mL) at Weeks 24 and 96 with RUKOBIA (600 mg Twice Daily) plus OBT (Randomized Cohort) in BRIGHTE Trial (ITT-E Population, Snapshot Algorithm)
 | RUKOBIA 600 mg Twice Daily plus OBT
 | Week 24; (n = 272) | Week 96; (n = 272)
HIV-1 RNA <40 copies/mL | 53% | 60%
HIV-1 RNA ≥40 copies/mL | 40% | 30%
Data in window not <40 copies/mL | 32% | 12%
Discontinued for lack of efficacy | <1% | 4%
Discontinued for other reasons while not suppressed | 1% | 6%
Change in antiretroviral treatment regimen | 6% | 8%
No virologic data | 7% | 10%
Reasons:
Discontinued study/study drug due to adverse event or death | 4% | 6%
Discontinued study/study drug for other reasons | 2% | 3%
Missing data during window but on study | 1% | 2%

OBT = Optimized background therapy.

Table 13. Virologic Outcomes (HIV-1 RNA <40 copies/mL) by Baseline Covariates at Weeks 24 and 96 with RUKOBIA (600 mg Twice Daily) plus OBT (Randomized Cohort) in BRIGHTE Trial (ITT-E Population, Snapshot Algorithm)
 | RUKOBIA 600 mg Twice Daily plus OBT
 | Week 24; (n = 272) | Week 96; (n = 272)
Baseline plasma viral load (copies/mL)
<100,000 | 60% (116/192) | 65% (124/192)
≥100,000 | 35% (28/80) | 49% (39/80)
Baseline CD4+ (cells/mm^3)
<20 | 32% (23/72) | 46% (33/72)
20 to <50 | 48% (12/25) | 56% (14/25)
50 to <200 | 58% (59/102) | 61% (62/102)
≥200 | 68% (50/73) | 74% (54/73)
Number of fully active and available antiretroviral classes in initial background regimen
0a | 31% (5/16) | 19% (3/16)
1 | 56% (80/142) | 65% (92/142)
2 | 52% (59/114) | 60% (68/114)
Use of DTG and DRVb as a component of OBT
DTG and DRV | 58% (68/117) | 64% (75/117)
With DTG, without DRV | 54% (61/112) | 63% (71/112)
Without DTG, with DRV | 29% (5/17) | 47% (8/17)
Without DTG/DRV | 38% (10/26) | 35% (9/26)
Gender
Male | 52% (104/200) | 59% (118/200)
Female | 56% (40/72) | 63% (45/72)
Race
White | 49% (90/185) | 56% (103/185)
Black or African-American/Others | 62% (54/87) | 69% (60/87)
Age (years)
<50 | 50% (81/162) | 59% (96/162)
≥50 | 57% (63/110) | 61% (67/110)
OBT = Optimized background therapy; DTG = Dolutegravir; DRV = Darunavir.
a Includes subjects who never initiated OBT, were incorrectly assigned to the randomized cohort, or had 1 or more active antiretroviral agents available at screening but did not use these as part of the initial OBT.
b Darunavir was coadministered with ritonavir or cobicistat.

In the randomized cohort, HIV-1 RNA <200 copies/mL was achieved in 68% and 64% of subjects at Weeks 24 and 96, respectively (ITT-E, Snapshot algorithm). Mean changes in CD4+ cell count from baseline increased over time: 90 cells/mm^3 at Week 24 and 205 cells/mm^3 at Week 96. Based on a sub-analysis in the randomized cohort, subjects with the lowest baseline CD4+ cell counts (<20 cells/mm^3) had a similar increase in CD4+ cell count over time compared with subjects with higher baseline CD4+ cell count (>200 to <500 cells/mm^3).

Nonrandomized Cohort

In the nonrandomized cohort, HIV-1 RNA <40 copies/mL was achieved in 37% of subjects at Weeks 24 and 96. At these timepoints, the proportion of subjects with HIV-1 RNA <200 copies/mL was 42% and 39%, respectively (ITT-E, Snapshot algorithm). Mean changes in CD4+ cell count from baseline increased over time: 41 cells/mm^3 at Week 24 and 119 cells/mm^3 at Week 96.

16 HOW SUPPLIED/STORAGE AND HANDLING

RUKOBIA extended-release tablets, 600 mg, are beige, oval, film-coated, biconvex tablets debossed with “SV 1V7” on one side.

Bottle of 60 tablets with child-resistant closure. NDC 49702-250-18.

Store at 20°C to 25°C (68°F to 77°F); excursions permitted between 15°C and 30°C (59°F and 86°F) [See USP Controlled Room Temperature].

RUKOBIA extended-release tablets may have a slight vinegar-like odor.

17 PATIENT COUNSELING INFORMATION

Advise the patient to read the FDA-approved patient labeling (Patient Information).

Hypersensitivity Reactions

Inform patients that if they have had a hypersensitivity reaction to RUKOBIA or any of its components, they should not take RUKOBIA [see Contraindications (4)].

Immune Reconstitution Syndrome

Advise patients to inform their healthcare provider immediately of any signs and symptoms of infection, as inflammation from previous infection may occur soon after combination antiretroviral therapy, including when RUKOBIA is started [see Warnings and Precautions (5.1)].

QTc Interval Prolongation

Advise patients that RUKOBIA may produce changes in their electrocardiogram (i.e., QT prolongation). Instruct patients to consult their healthcare provider if they experience symptoms such as dizziness, lightheadedness, abnormal heart rhythm, or loss of consciousness [see Warnings and Precautions (5.2)].

Patients with Hepatitis B or C Virus Co-Infection

Advise patients that it is recommended to have laboratory testing and to take medications for HBV or HCV as prescribed [see Warnings and Precautions (5.3)].

Drug Interactions

RUKOBIA may interact with other drugs; therefore, advise patients to report to their healthcare provider the use of any other prescription or nonprescription medication or herbal products, including St. John’s wort [see Contraindications (4), Warnings and Precautions (5.4), Drug Interactions (7)].

Pregnancy Registry

Inform patients that there is an antiretroviral pregnancy registry to monitor fetal outcomes in those exposed to RUKOBIA during pregnancy [see Use in Specific Populations (8.1)].

Lactation

Inform individuals with HIV-1 infection that the potential risks of breastfeeding include: (1) HIV-1 transmission (in HIV-1–negative infants), (2) developing viral resistance (in HIV-1–positive infants), and (3) adverse reactions in a breastfed infant similar to those seen in adults [see Use in Specific Populations (8.2)].

Potential Odor of Tablets

RUKOBIA tablets may have a slight vinegar-like odor [see How Supplied/Storage and Handling (16)].

Missed Dosage

Advise patients to avoid missing doses as it can result in development of resistance. Instruct patients that if they miss a dose of RUKOBIA, to take it as soon as they remember. Advise patients not to double their next dose or take more than the prescribed dose [see Dosage and Administration (2)].

Trademark is owned by or licensed to the ViiV Healthcare group of companies.

Manufactured for:

ViiV Healthcare
Durham, NC 27701

©2024 ViiV Healthcare group of companies or its licensor.

RKB:3PI

PATIENT INFORMATION

RUKOBIA (rue-KOH-bee-ah)
(fostemsavir)
extended-release tablets

What is RUKOBIA?

RUKOBIA is a prescription medicine that is used with other human immunodeficiency virus-1 (HIV-1) medicines to treat HIV-1 infection in adults who:

- have received several HIV-1 medicines in the past, and
- have HIV-1 virus that is resistant to many HIV-1 medicines, and
- are failing their current HIV-1 medicines. Your HIV-1 medicines could be failing because they are not working or no longer work, you are not able to tolerate the side effects, or there are other safety reasons why you cannot take them.

HIV-1 is the virus that causes Acquired Immune Deficiency Syndrome (AIDS).

It is not known if RUKOBIA is safe and effective in children.

Do not take RUKOBIA if you:

- are allergic to fostemsavir or any of the ingredients in RUKOBIA. See the end of this leaflet for a complete list of ingredients in RUKOBIA.
- take certain medicines, including:

- enzalutamide
- carbamazepine
- phenytoin

- rifampin
- mitotane
- St. John’s wort (Hypericum perforatum)

Before taking RUKOBIA, tell your healthcare provider about all of your medical conditions, including if you:

- have or have had a heart problem, including a heart rhythm problem called QTc prolongation (irregular heartbeat).
- have or have had liver problems, including hepatitis B or C virus infection.
- are pregnant or plan to become pregnant. It is not known if RUKOBIA will harm your unborn baby. Tell your healthcare provider if you become pregnant during treatment with RUKOBIA.
  Pregnancy Exposure Registry. There is a pregnancy exposure registry for those who take RUKOBIA during pregnancy. The purpose of this registry is to collect information about the health of you and your baby. Talk to your healthcare provider about how you can take part in this registry.
- are breastfeeding or plan to breastfeed. RUKOBIA may pass into your breast milk. Talk with your healthcare provider about the following risks to your baby from breastfeeding during treatment with RUKOBIA:
  - the HIV-1 virus may pass to your baby if your baby does not have HIV-1 infection.
  - the HIV-1 virus may become harder to treat if your baby has HIV-1 infection.
  - your baby may get side effects from RUKOBIA.

Tell your healthcare provider about all the medicines you take, including prescription and over-the-counter medicines, vitamins, and herbal supplements.

Some medicines interact with RUKOBIA.

Keep a list of your medicines and show it to your healthcare provider and pharmacist when you get a new medicine.

- You can ask your healthcare provider or pharmacist for a list of medicines that interact with RUKOBIA.
- Do not start taking a new medicine without telling your healthcare provider. Your healthcare provider can tell you if it is safe to take RUKOBIA with other medicines.

Especially tell your healthcare provider if you take birth control pills (oral contraceptives) that contain ethinyl estradiol. The amount of ethinyl estradiol can become increased in your blood during treatment with RUKOBIA. Talk to your healthcare provider about which oral contraceptives may be right for you during treatment with RUKOBIA.

How should I take RUKOBIA?

- Take RUKOBIA exactly as your healthcare provider tells you to take it.
- Take RUKOBIA tablets whole. Do not chew, crush, or split RUKOBIA tablets before swallowing.
- Take RUKOBIA with or without food.
- RUKOBIA tablets may have a slight odor (like vinegar). This is normal.
- Do not miss a dose of RUKOBIA. If you miss a dose of RUKOBIA, take it as soon as you remember. Do not take 2 doses at the same time or take more than your healthcare provider tells you to take.
- Do not run out of RUKOBIA. The virus in your blood may increase and the virus may become harder to treat. When your supply starts to run low, get more from your healthcare provider or pharmacy.
- If you take too much RUKOBIA, call your healthcare provider or go to the nearest hospital emergency room right away.

What are the possible side effects of RUKOBIA?

RUKOBIA can cause serious side effects including:

- Changes in your immune system (Immune Reconstitution Syndrome) can happen when you start taking HIV-1 medicines. Your immune system may get stronger and begin to fight infections that have been hidden in your body for a long time. Tell your healthcare provider right away if you start having new symptoms after you start taking RUKOBIA.
- Heart rhythm problems (QTc prolongation). RUKOBIA may cause a heart rhythm problem called QTc prolongation. QTc prolongation causes an irregular heartbeat. If you are elderly, or if you take certain other medicines, you may be at a greater risk for developing this heart problem with RUKOBIA.
  Tell your healthcare provider right away if you feel dizzy, lightheaded, feel changes in your heartbeat, or you faint (lose consciousness).
- Changes in liver function blood tests results. People with HIV-1 who take RUKOBIA and who also have hepatitis B or C virus infections, may be more likely to develop new or worsening changes in certain liver function blood tests during treatment with RUKOBIA.
  - If you stop your anti-hepatitis B treatment, this could mean that your hepatitis B may become active again (reactivated). Your healthcare provider may do blood tests to check your liver during treatment with RUKOBIA especially if you have hepatitis B virus infection.
  - Take any anti-hepatitis B or anti-hepatitis C medicines as prescribed by your healthcare provider during treatment with RUKOBIA.

The most common side effect of RUKOBIA is nausea.

These are not all of the possible side effects of RUKOBIA.

Call your doctor for medical advice about side effects. You may report side effects to FDA at 1‑800‑FDA‑1088.

How should I store RUKOBIA?

- Store RUKOBIA at room temperature between 68°F to 77°F (20°C to 25°C).
- RUKOBIA comes in a child-resistant package.

Keep RUKOBIA and all medicines out of the reach of children.

General information about the safe and effective use of RUKOBIA.

Medicines are sometimes prescribed for purposes other than those listed in a Patient Information leaflet. Do not use RUKOBIA for a condition for which it was not prescribed. Do not give RUKOBIA to other people, even if they have the same symptoms you have. It may harm them. You can ask your pharmacist or healthcare provider for information about RUKOBIA that is written for health professionals.

What are the ingredients in RUKOBIA?

Active ingredient: fostemsavir tromethamine

Inactive ingredients: colloidal silicon dioxide, hydroxypropyl cellulose, hypromellose, and magnesium stearate.

The tablet film-coating contains iron oxide red, iron oxide yellow, polyethylene glycol, polyvinyl alcohol, talc, and titanium dioxide.

Manufactured for:
ViiV Healthcare
Durham, NC 27701

Trademark is owned by or licensed to the ViiV Healthcare group of companies.

©2024 ViiV Healthcare group of companies or its licensor.

RKB:2PIL

For more information, go to www.RUKOBIA.com or call 1-877-844-8872.

This Patient Information has been approved by the U.S. Food and Drug Administration. Revised: 02/2024

PACKAGE LABEL

PRINCIPAL DISPLAY PANEL

NDC 49702-250-18

Rukobia

(fostemsavir)

600 mg

extended-release tablets

Rx Only

Each film-coated tablet contains 600 mg of fostemsavir (equivalent to 725 mg fostemsavir tromethamine).

Bottle of 60 tablets

ViiV Healthcare

Note to pharmacist:

Do not cover ALERT box with pharmacy label.

ALERT: Find out about medicines that should NOT be taken with RUKOBIA.

Made in UK

©2024 ViiV Healthcare group of companies or its licensor.

Rev. 5/24

62000000093939